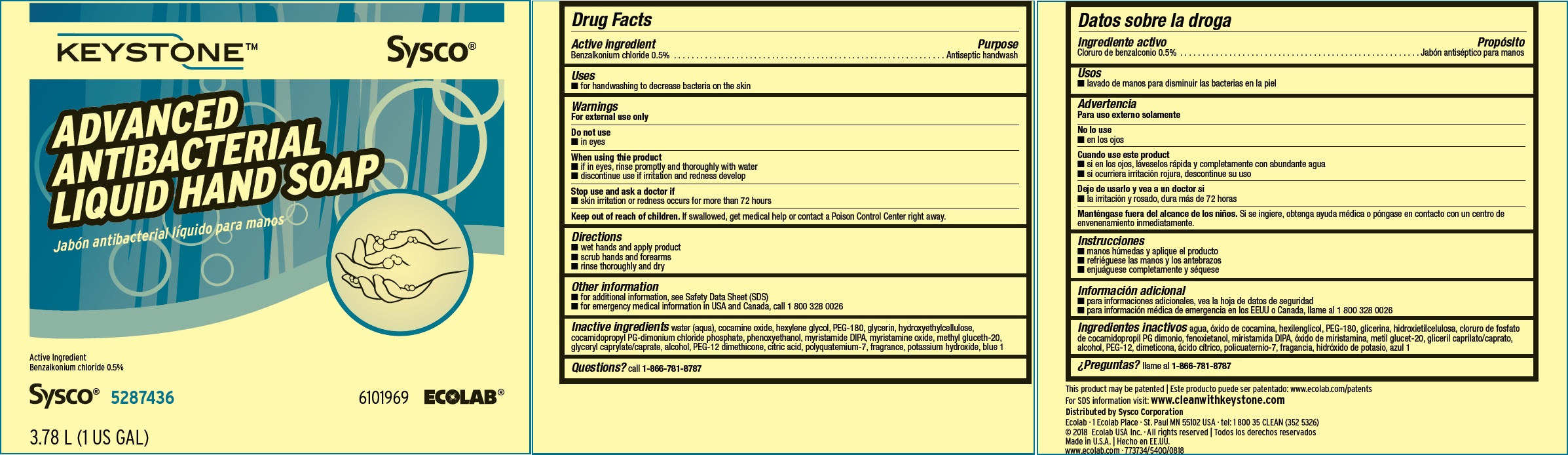 DRUG LABEL: Keystone
NDC: 47593-594 | Form: SOLUTION
Manufacturer: Ecolab Inc.
Category: otc | Type: HUMAN OTC DRUG LABEL
Date: 20240805

ACTIVE INGREDIENTS: BENZALKONIUM CHLORIDE 5 mg/1 mL
INACTIVE INGREDIENTS: WATER; COCAMINE OXIDE; HEXYLENE GLYCOL; POLYETHYLENE GLYCOL 8000; GLYCERIN; HYDROXYETHYL CELLULOSE (4000 MPA.S AT 1%); COCAMIDOPROPYL PG-DIMONIUM CHLORIDE PHOSPHATE; PHENOXYETHANOL; MYRISTIC DIISOPROPANOLAMIDE; MYRISTAMINE OXIDE; METHYL GLUCETH-20; GLYCERYL MONO- AND DICAPRYLOCAPRATE; ALCOHOL; PEG-12 DIMETHICONE (300 CST); ANHYDROUS CITRIC ACID; POLYQUATERNIUM-7 (70/30 ACRYLAMIDE/DADMAC; 1600000 MW); POTASSIUM HYDROXIDE; FD&C BLUE NO. 1

Drug Facts

Active ingredient

Benzalkonium Chloride, 0.5%

Purpose

Antiseptic handwash

Uses

for handwashing to decrease bacteria on the skin

Warnings

For external use only

Do not use

- in eyes

When using the product

- if in eyes, rinse promptly and thoroughly with water
- discontinue use if irritation and redness develop

Stop use and ask a doctor if skin irritation or redness occurs for more than 72 hours

Keep out of reach of children. If swallowed, get medical help or contact a Poison Control Center right away.

Directions

- wet hands and apply product
- scrub hands and forearms
- rinse thoroughly and dry

Other information

- for additional information, see Safety Data Sheet (SDS)
- for emergency medical information in USA and Canada, call 1 800 328 0026

INACTIVE INGREDIENT

Inactive ingredients water (aqua), cocamine oxide, hexylene glycol, PEG-180, glycerin, hydroxyethylcellulose, cocamidopropyl PG-dimonium chloride phosphate, phenoxyethanol, myristamide DIPA, myristamine oxide, methyl gluceth-20, glyceryl caprylate/caprate, alcohol, PEG-12 dimethicone, citric acid, polyquatemium-7, fragrance, potassium hydroxide, blue 1

Questions? call 1-866-781-8787

Principal display panel and representative label

KEYSTONE Sysco

ADVANCED ANTIBACTERIAL LIQUID HAND SOAP

Active Ingredient: 0.5% Benzalkonium Chloride

Net Contents

750 mL (25 US fl oz) 6000234

Sysco 5287436 6101969 ECOLAB®

This product may be patented: www.ecolab.com/patents

For SDS information visit: www.cleanwithkeystone.com

Ecolab · 1 Ecolab Place · St. Paul MN 55102 USA · tel: 1 800 35 CLEAN (352 5326)

© 2018 Ecolab USA Inc. · All rights reserved

Made in U.S.A.

www.ecolab.com · 773734/5400/0818